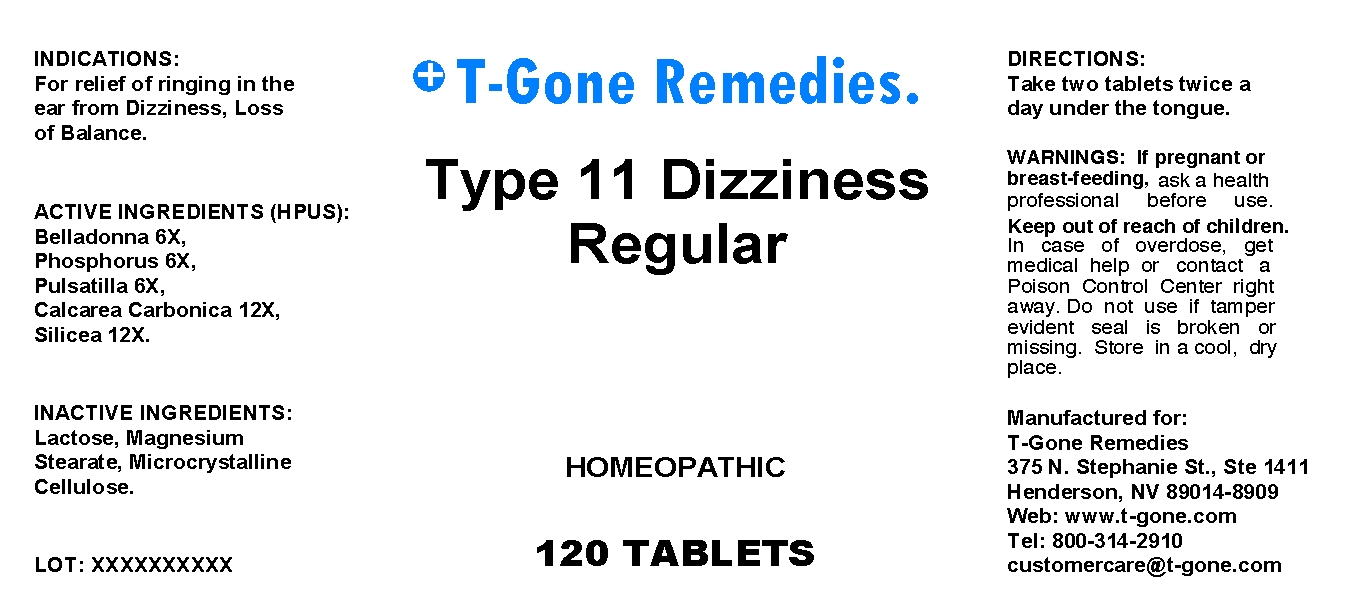 DRUG LABEL: Type 11 Dizziness Regular
NDC: 57520-0431 | Form: TABLET
Manufacturer: Apotheca Company
Category: homeopathic | Type: HUMAN OTC DRUG LABEL
Date: 20100715

ACTIVE INGREDIENTS: ATROPA BELLADONNA 6 [hp_X]/1 mg; PHOSPHORUS 6 [hp_X]/1 mg; PULSATILLA VULGARIS 6 [hp_X]/1 mg; OYSTER SHELL CALCIUM CARBONATE, CRUDE 12 [hp_X]/1 mg; SILICON DIOXIDE 12 [hp_X]/1 mg
INACTIVE INGREDIENTS: LACTOSE; MAGNESIUM STEARATE; CELLULOSE, MICROCRYSTALLINE

Type 11 Dizziness Regular

ACTIVE INGREDIENT

ACTIVE INGREDIENTS: Belladonna 6X, Phosphorus 6X, Pulsatilla 6X, Calcarea carbonica 12X, Silicea 12X.

PURPOSE

INDICATIONS: For relief of ringing in the ear from Dizziness, Loss of Balance.

WARNINGS

WARNINGS: If pregnant or breast-feeding, ask a health professional before use.

Keep out of reach of children. In case of overdose, get medical help or contact a Poison Control Center right away.

Do not use if tamper evident seal is broken or missing. Store in a cool, dry place.

DOSAGE AND ADMINISTRATION

DIRECTIONS: Take two tablets twice a day under the tongue.

INACTIVE INGREDIENT

INACTIVE INGREDIENTS: Lactose, Magnesium stearate, Microcrystalline cellulose.

QUESTIONS

Manufactured for:

T-Gone Remedies.

375 N. Stephanie St., Ste 1411

Henderson, NV 89014-8909

Web: www.t-gone.com

Tel: 800-314-2910

customercare@t-gone.com

PACKAGE LABEL

T-Gone Remedies.

Type 11 Dizziness Regular

HOMEOPATHIC

120 TABLETS